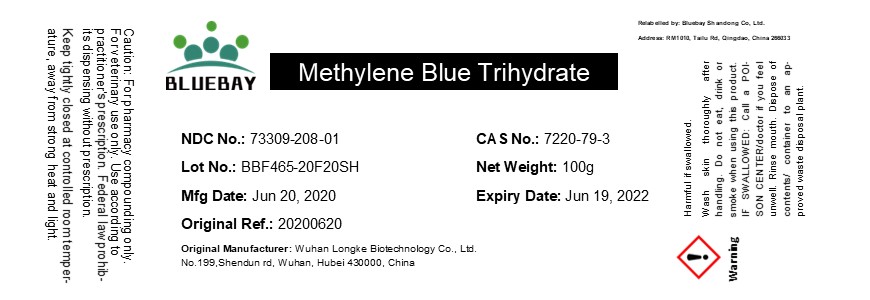 DRUG LABEL: Methylene Blue Trihydrate
NDC: 73309-208 | Form: POWDER
Manufacturer: BLUEBAY SHANDONG CO.,LTD
Category: other | Type: BULK INGREDIENT
Date: 20201104

ACTIVE INGREDIENTS: METHYLENE BLUE 1 g/1 g

Methylene Blue Trihydrate